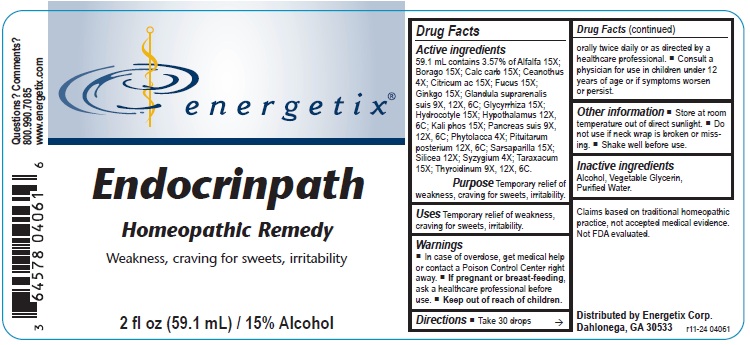 DRUG LABEL: Endocrinpath
NDC: 64578-0101 | Form: LIQUID
Manufacturer: Energetix Corporation
Category: homeopathic | Type: HUMAN OTC DRUG LABEL
Date: 20250711

ACTIVE INGREDIENTS: ALFALFA 15 [hp_X]/1 mL; BORAGE 15 [hp_X]/1 mL; OYSTER SHELL CALCIUM CARBONATE, CRUDE 15 [hp_X]/1 mL; CEANOTHUS AMERICANUS LEAF 4 [hp_X]/1 mL; ANHYDROUS CITRIC ACID 15 [hp_X]/1 mL; FUCUS VESICULOSUS 15 [hp_X]/1 mL; GINKGO 15 [hp_X]/1 mL; SUS SCROFA ADRENAL GLAND 9 [hp_X]/1 mL; GLYCYRRHIZA GLABRA 15 [hp_X]/1 mL; CENTELLA ASIATICA 15 [hp_X]/1 mL; BOS TAURUS HYPOTHALAMUS 12 [hp_X]/1 mL; POTASSIUM PHOSPHATE, DIBASIC 15 [hp_X]/1 mL; SUS SCROFA PANCREAS 9 [hp_X]/1 mL; PHYTOLACCA AMERICANA ROOT 4 [hp_X]/1 mL; BOS TAURUS PITUITARY GLAND 12 [hp_X]/1 mL; SMILAX ORNATA ROOT 15 [hp_X]/1 mL; SILICON DIOXIDE 12 [hp_X]/1 mL; SYZYGIUM CUMINI SEED 4 [hp_X]/1 mL; TARAXACUM OFFICINALE 15 [hp_X]/1 mL; THYROID, BOVINE 9 [hp_X]/1 mL
INACTIVE INGREDIENTS: WATER; GLYCERIN; ALCOHOL

Endocrinpath

ACTIVE INGREDIENT

Active ingredients59.1 mL contains 3.57% of: Alfalfa 15X; Borago 15X; Calc carb 15X; Ceanothus 4X; Citricum ac 15X; Fucus 15X; Ginkgo 15X; Glandula suprarenalis suis 9X, 12X, 6C; Glycyrrhiza 15X; Hydrocotyle 15X; Hypothalamus 12X, 6C; Kali phos 15X; Pancreas suis 9X, 12X, 6C; Phytolacca 4X; Pituitarum posterium 12X, 6C; Sarsaparilla 15X; Silicea 12X; Syzygium 4X; Taraxacum 15X; Thyroidinum 9X, 12X, 6C

Claims based on traditional homeopathic practice, not accepted medical evidence. Not FDA evaluated.

Uses

Temporary relief of weakness, craving for sweets, irritability.

Warnings

- In case of overdose, get medical help or contact a Poison Control Center right away.
- If pregnant or breast feeding, ask a healthcare professional before use.

• Keep out of reach of children.

Directions

- Take 30 drops orally twice daily or as directed by a healthcare professional.
- Consult a physician for use in children under 12 years of age or if symptoms worsen or persist.

Other information

- Store at room temperature out of direct sunlight.
- Do not use if neck wrap is broken or missing.
- Shake well before use.

Inactive ingredients

Alcohol, Vegetable Glycerin, Purified Water.

QUESTIONS

Distributed by Energetix Corp.

Dahlonega, GA 30533

Questions? Comments?

800.990.7085 www.energetix.com

PACKAGE LABEL

energetix

Endocrinpath

Homeopathic Remedy

Weakness, craving for sweets, irritability

2 fl oz (59.1 mL) / 15% Alcohol

PURPOSE

Purpose Temporary relief of weakness, craving for sweets, irritability.